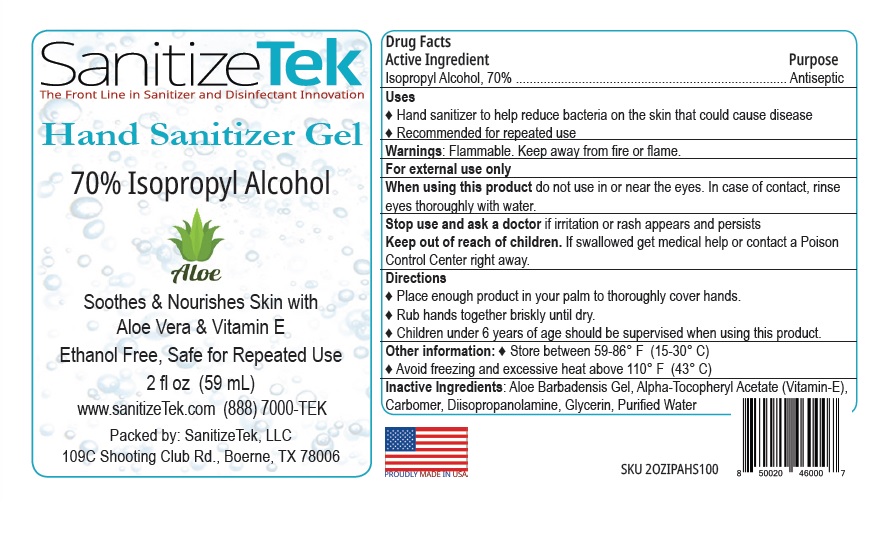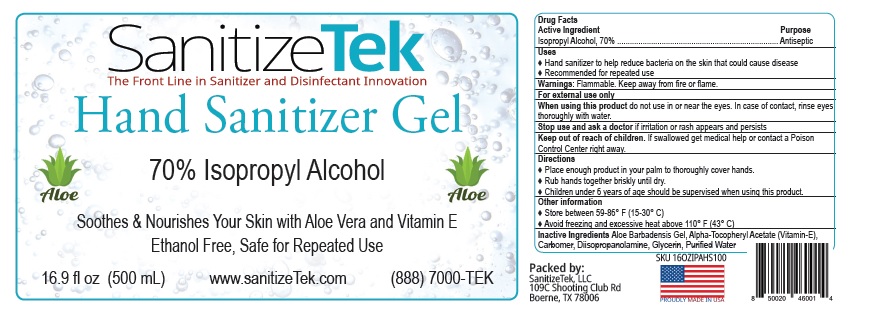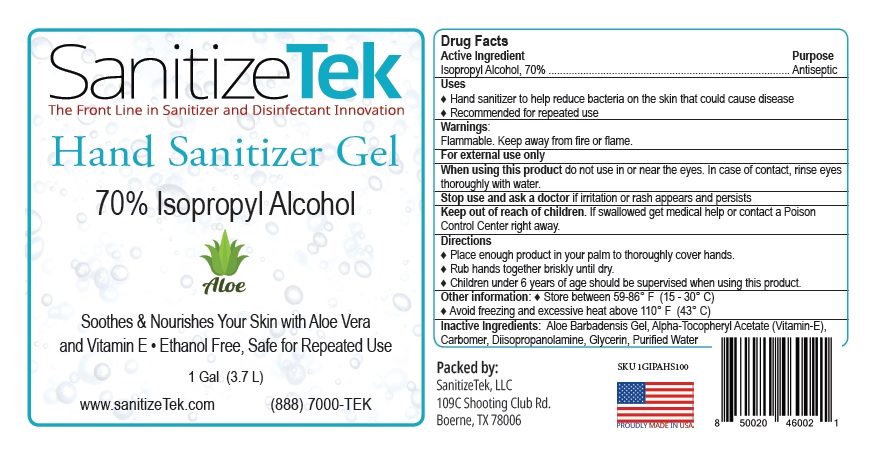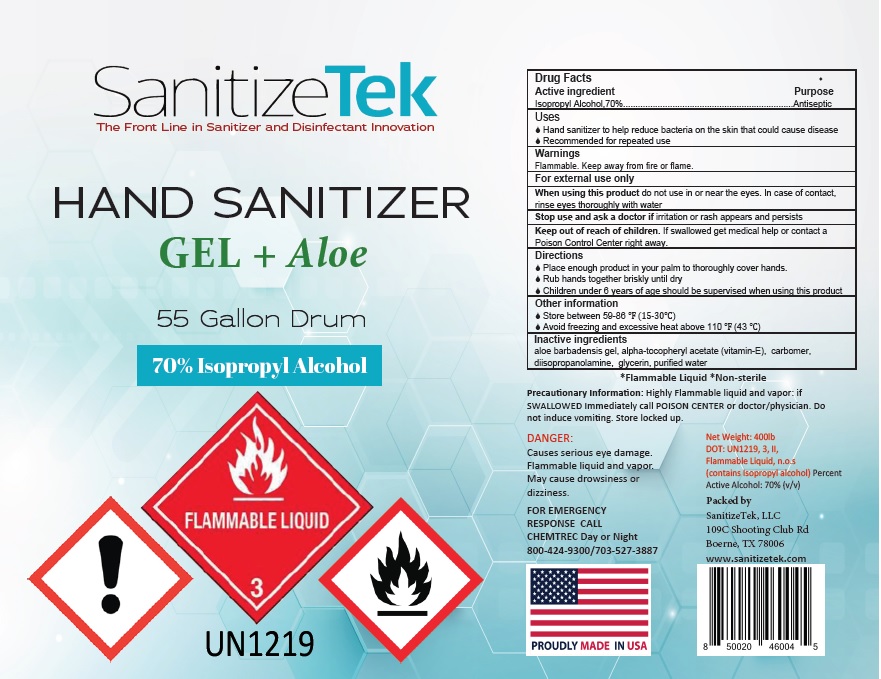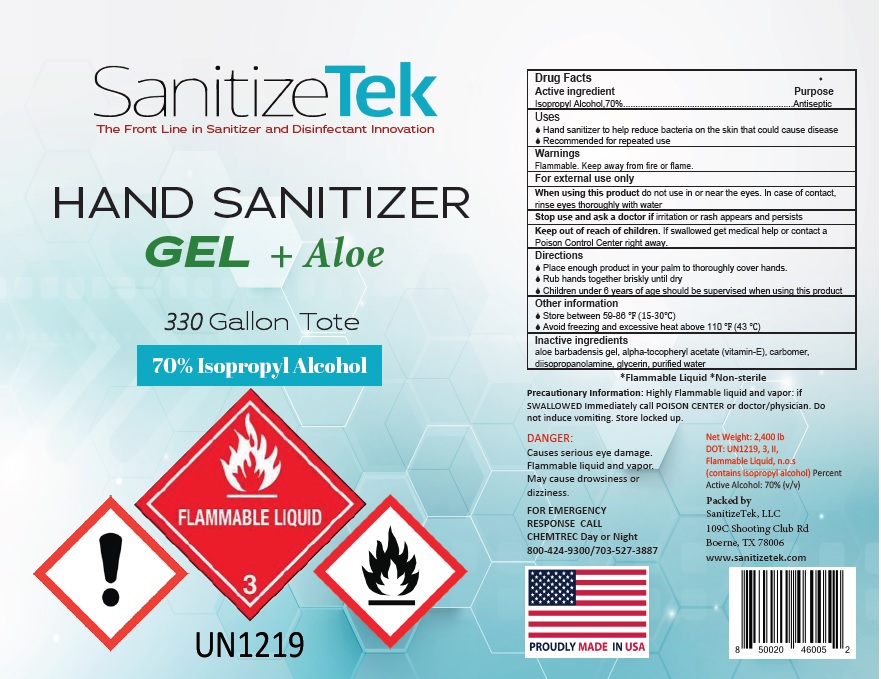 DRUG LABEL: Sanitizetek Gel
NDC: 81737-001 | Form: GEL
Manufacturer: Sanitizetek, LLC
Category: otc | Type: HUMAN OTC DRUG LABEL
Date: 20210408

ACTIVE INGREDIENTS: ALCOHOL 0.700 L/1 L
INACTIVE INGREDIENTS: ALOE VERA LEAF; .ALPHA.-TOCOPHEROL ACETATE; CARBOMER HOMOPOLYMER, UNSPECIFIED TYPE; DIISOPROPANOLAMINE; GLYCERIN; WATER

SanitizeTek Hand Sanitizer Gel

Drug Facts

Active Ingredient
Isopropyl Alcohol, 70%

Purpose
Antiseptic

Uses
♦ Hand sanitizer to help reduce bacteria on the skin that could cause disease
♦ Recommended for repeated use

Warnings: Flammable. Keep away from fire or flame.
For external use only
When using this product do not use in or near the eyes. In case of contact, rinse eyes thoroughly with water.
Stop use and ask a doctor if irritation or rash appears and persists

Keep out of reach of children. If swallowed, get medical help or contact a Poison Control Center right away.

Directions

♦ Place enough product in your palm to thoroughly cover hands.
♦ Rub hands together briskly until dry.
♦ Children under 6 years of age should be supervised when using this product.

Other information

♦ Store between 59-86º F (15 - 30° C)
♦ Avoid freezing and excessive heat above 110º F (43º C)

INACTIVE INGREDIENT

Inactive Ingredients: Aloe Barbadensis Gel, Alpha-Tocopheryl Acetate (Vitamin-E),

Carbomer, Diisopropanolamine, Glycerin, Purified Water

Package Label

SanitizeTek

The Front Line in Sanitizer and Disinfectant Innovation

Hand Sanitizer Gel
70% Isopropyl Alcohol

Alor

Soothes & Nourishes Skin with

Aloe Vera & Vitamin E

Ethanol Free, Safe for Repeated Use

2 fl oz (59 mL)

www.sanitizeTek.com (888) 7000-TEK

Packed by: SanitizeTek, LLC
109C Shooting Club Rd., Boerne, TX 78006

2 OZ

16.9 OZ

1 GAL

55 GAL

330 GAL

res